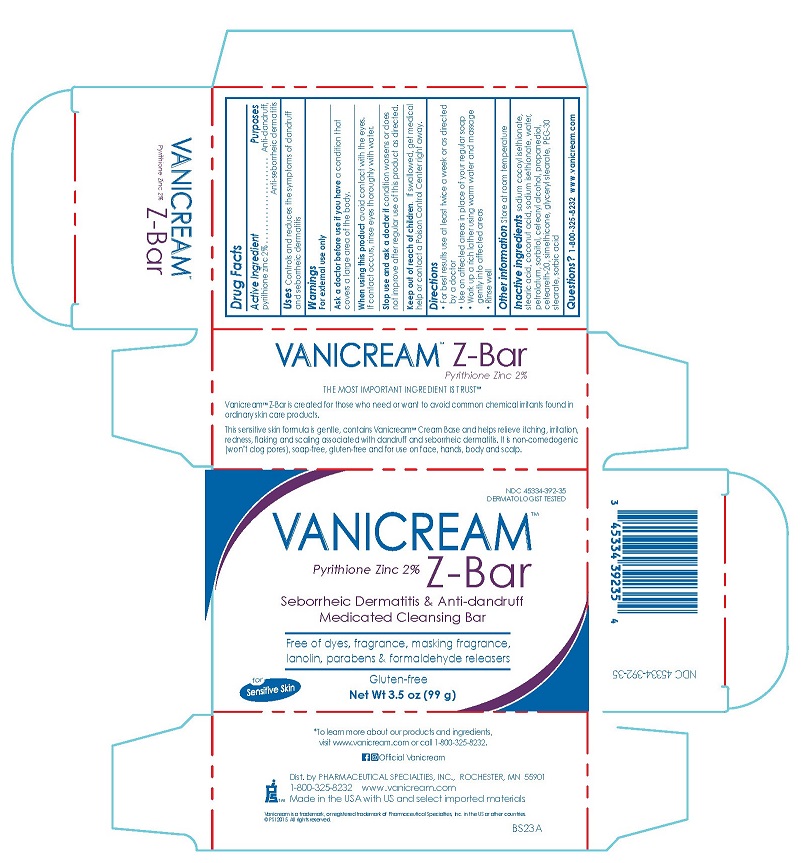 DRUG LABEL: Vanicream Z-Bar
NDC: 45334-392 | Form: SOAP
Manufacturer: Pharmaceutical Specialties, Inc.
Category: otc | Type: HUMAN OTC DRUG LABEL
Date: 20241003

ACTIVE INGREDIENTS: PYRITHIONE ZINC 2 g/100 g
INACTIVE INGREDIENTS: SODIUM COCOYL ISETHIONATE; PROPANEDIOL; POLYOXYL 20 CETOSTEARYL ETHER; PEG-30 STEARATE; WATER; COCONUT ACID; DIMETHICONE, UNSPECIFIED; SORBIC ACID; CETOSTEARYL ALCOHOL; GLYCERYL MONOSTEARATE; SORBITOL; STEARIC ACID; PETROLATUM; SODIUM ISETHIONATE

Vanicream Z-Bar

Active ingredient

pyrithione zinc 2%

Purposes

Anti-dandruff, Anti-seborrheic dermatitis

INDICATIONS AND USAGE

Uses Controls and reduces the symptoms of dandruff and seborrheic dermatitis

Warnings

For external use only

Ask a doctor before use if you have a condition that covers a large area of the body.

When using this product avoid contact with the eyes. If contact occurs, rinse eyes thoroughly with water.

Stop use and ask a doctor if condition worsens or does not improve after regular use of this product as directed.

Keep out of reach of children. If swallowed, get medical help or contact a Poison Control Center right away.

Directions

- For best results use at least twice a week or as directed by a doctor
- Use on affected areas in place of your regular soap
- Work up a rich lather using warm water and massage gently into affected areas
- Rinse well

Other information

Store at room temperature

INACTIVE INGREDIENT

Inactive ingredients sodium cocoyl isethionate, stearic acid, coconut acid, sodium isethionate, water, petrolatum, sorbitol, cetearyl alcohol, propanediol, ceteareth-20, simethicone, glyceryl stearate, PEG-30 stearate, sorbic acid

Questions? 1-800-325-8232 www.vanicream.com

Dist. by PHARMACEUTICAL SPECIALTIES, INC. ROCHESTER, MN 55901

1-800-325-8232 www.vanicream.com

Made in the USA with US and select imported materials

PACKAGE LABEL

VANICREAM™ Z-Bar

Pyrithione Zinc 2%

NDC 45334-392-35

DERMATOLOGIST TESTED

Seborrheic Dermatitis & Anti-dandruff Medicated Cleansing Bar

for Sensitive Skin

Net Wt 3.5 oz (99g)